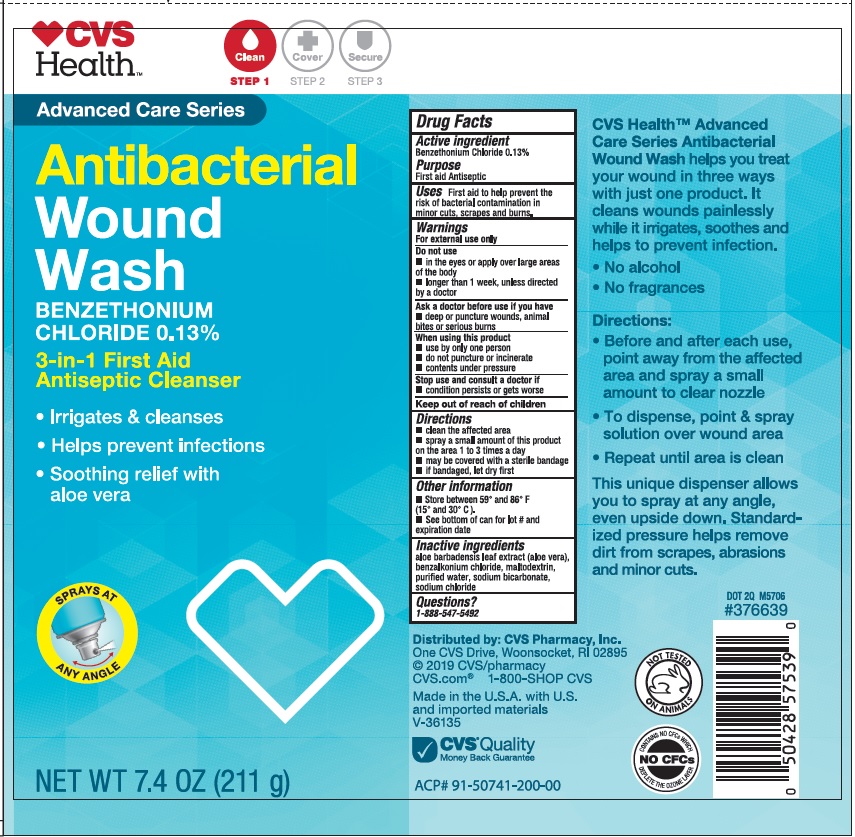 DRUG LABEL: CVS Antiseptic Wound Wash
NDC: 69842-327 | Form: SOLUTION
Manufacturer: CVS Pharmacy
Category: otc | Type: HUMAN OTC DRUG LABEL
Date: 20231122

ACTIVE INGREDIENTS: BENZETHONIUM CHLORIDE 1.3 mg/1 g
INACTIVE INGREDIENTS: ALOE VERA LEAF; BENZALKONIUM CHLORIDE; MALTODEXTRIN; WATER; SODIUM BICARBONATE; SODIUM CHLORIDE

CVS Antiseptic Wound Wash

Active ingredients

Benzethonium Chloride 0.13%

Purpose

First aid Antiseptic

Uses

First aid to help prevent the risk of bacterial contamination in minor cuts, scrapes and burns.

Warnings

For external use only

Do not use

- in the eyes or apply over large areas of the body
- longer than 1 week, unless directed by a doctor
- for single patient use only

Ask a doctor before use if you have

deep or puncture wounds, animal bites or serious burns

When using this product

- do not puncture or incinerate
- contents under pressure

Stop use and consult a doctor if

- condition persists or gets worse

Directions

- clean the affected area
- spray a small amount of this product on the area 1 to 3 times a day
- may be covered with a sterile bandage
- if bandaged, let dry first

Other information

- Store between 59° and 86° F (15° and 30° C).
- See bottom of can for lot # and expiration date

Inactive ingredients

aloe barbadensis leaf extract (aloe vera), benzalkonium chloride, maltodextrin, purified water, sodium bicarbonate, sodium chloride

Questions?

1-888-547-5492